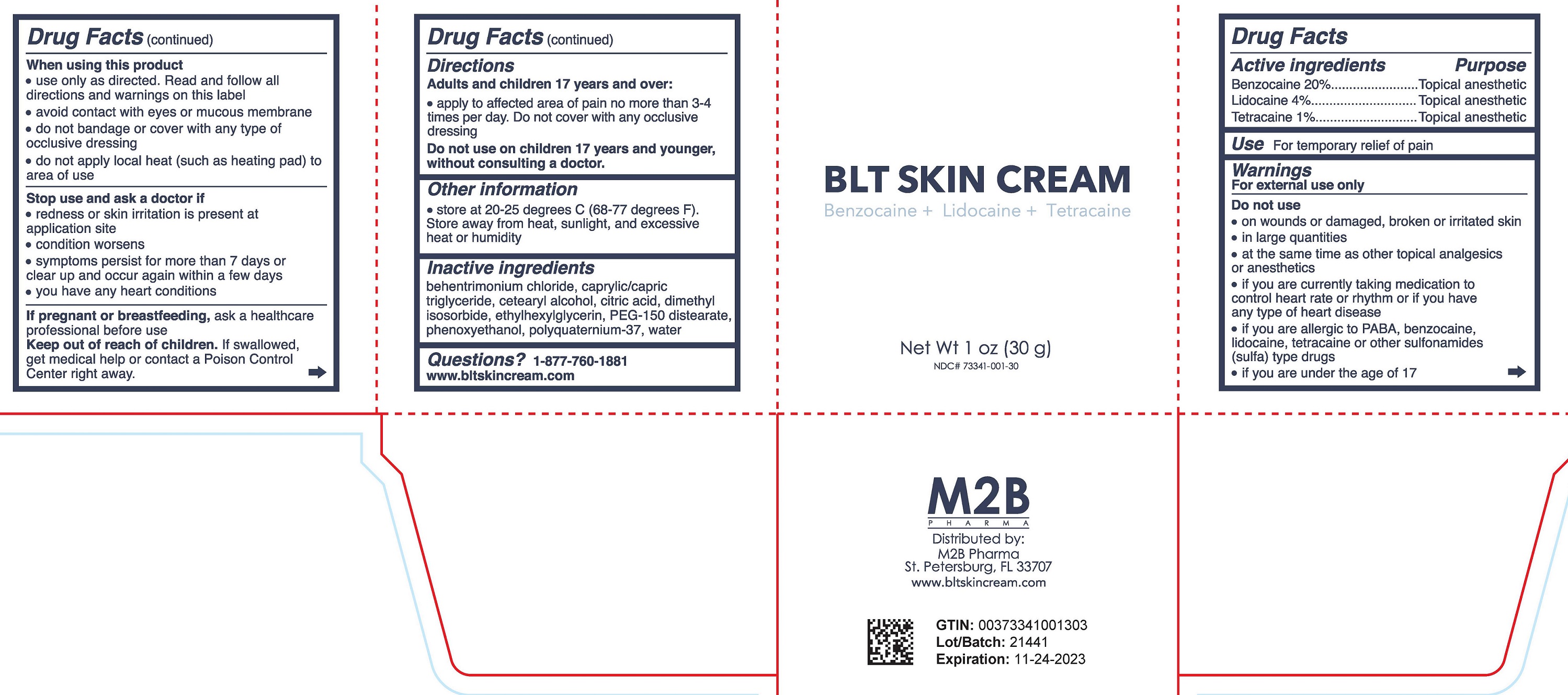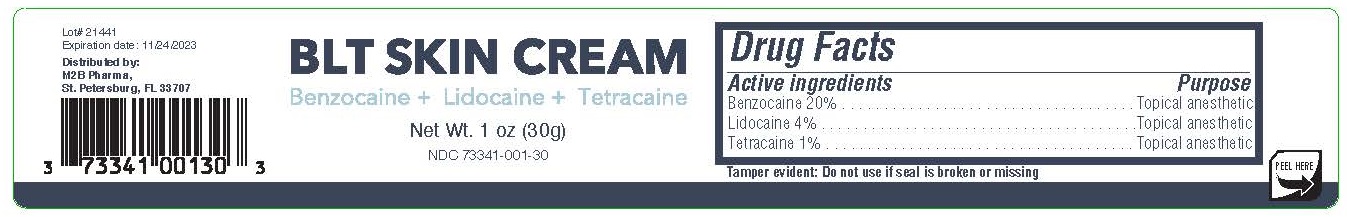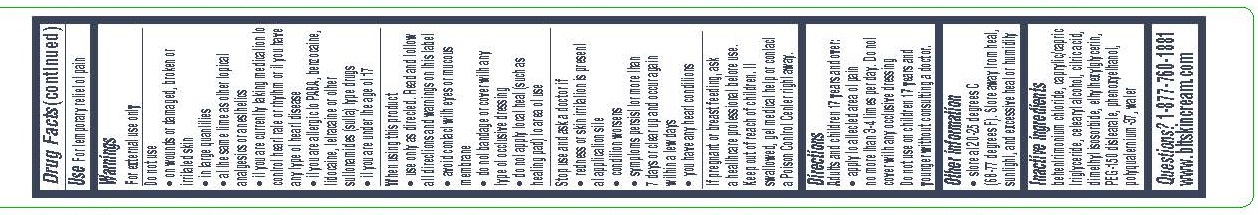 DRUG LABEL: BLT Skin Cream
NDC: 73341-001 | Form: CREAM
Manufacturer: M2B Pharma LLC
Category: otc | Type: HUMAN OTC DRUG LABEL
Date: 20251204

ACTIVE INGREDIENTS: BENZOCAINE 0.2 g/1 g; TETRACAINE 0.01 g/1 g; LIDOCAINE 0.04 g/1 g
INACTIVE INGREDIENTS: MEDIUM-CHAIN TRIGLYCERIDES; CETOSTEARYL ALCOHOL; DIMETHYL ISOSORBIDE; POLYQUATERNIUM 37 (200 MPA.S); BEHENTRIMONIUM CHLORIDE; CITRIC ACID MONOHYDRATE; WATER; ETHYLHEXYLGLYCERIN; PEG-150 DISTEARATE; PHENOXYETHANOL

BLT Skin Cream

Active ingredient

Benzocaine 20%

Purpose

Topical anesthetic

Active ingredient

Lidocaine 4%

Purpose

Topical analgesic

Active ingredient

Tetracaine 1%

Purpose

Topical analgesic

Uses

For temporary relief of pain

Warnings

For external use only

Do not use

- On wounds or damaged, broken or irritated skin
- In large quantities
- At the same time as other topical analgesics or anesthetics
- If you are currently taking medication to control heart rate or rhythm or if you have any type of heart disease
- If you are allergic to PABA, benzocaine, lidocaine, tetracaine or other sulfonamides (sulfa) type drugs
- If you are under the age of 17

When using this product

- Use only as directed. Read and follow all directions and warnings on this label.
- Avoid contact with eyes or mucous membrane
- Do not bandage or cover with any type of clear occlusive dressing
- Do not apply local heat (such as heating pad) to area of use

Stop use and ask a doctor if

- If redness or skin irritation is present at application site
- Condition worsens
- Symptoms persist for more than 7 days or clear up and occur again within a few days
- You have any heart conditions

If pregnant or breast-feeding,

ask a health professional before use.

Keep out of reach of children.

If swallowed, get medical help or contact a Poison Control Center right away.

Directions

Adults and children over 17 years of age:

- Apply to affected area of pain no more than 3-4 times per day. Do not cover with any occlusive dressing

Do not use on children 17 years and younger without consulting a doctor.

Other Information

- Store at 20-25 degrees C (68-77 degrees F).
- Store away from heat, sunlight, and excessive heat or humidity

Inactive Ingredients

behentrimonium chloride, caprylic/capric triglyceride, cetearyl alcohol, citric acid, dimethyl isosorbide, ethylhexylglycerin, PEG-150 distearate, phenoxyethanol, polyquaternium-37, water

Questions?

1-877-760-1881

www.bltskincream.com